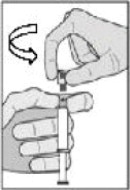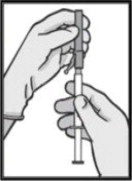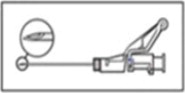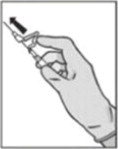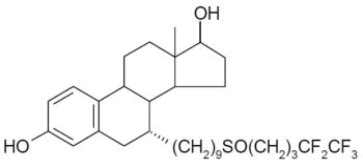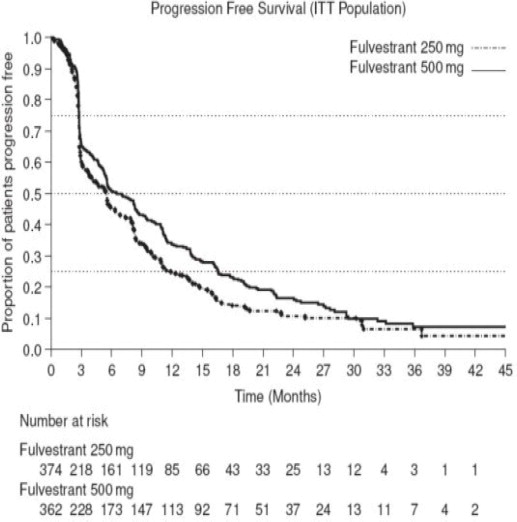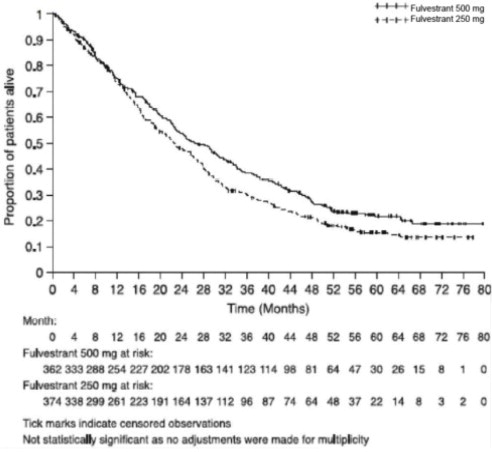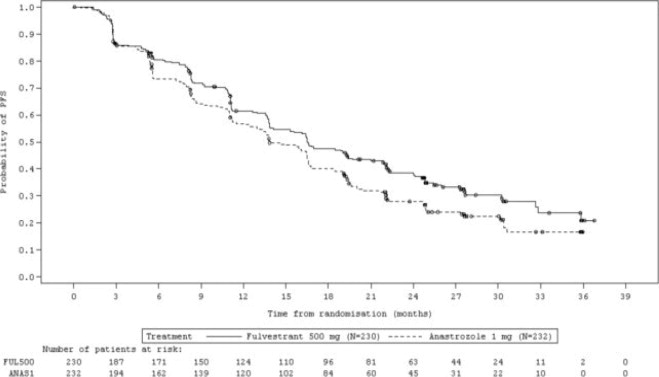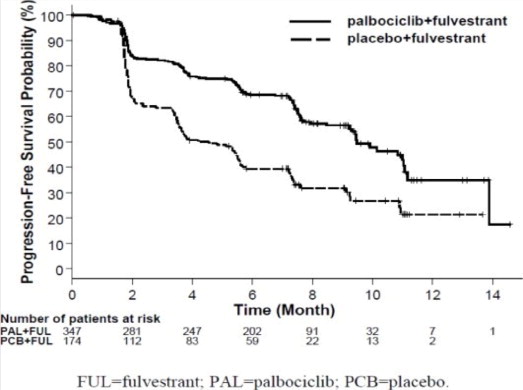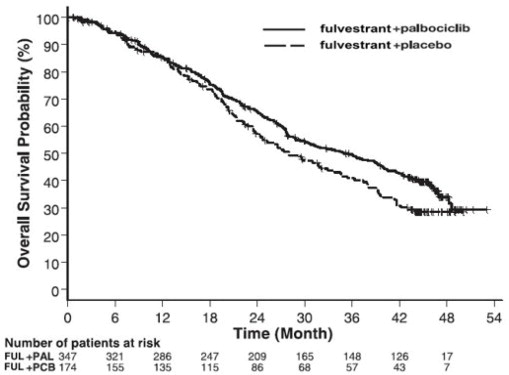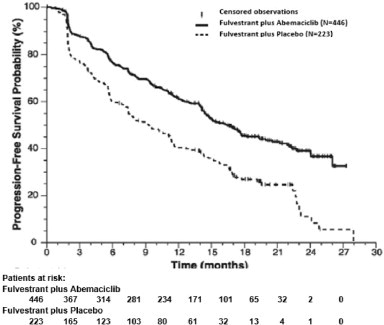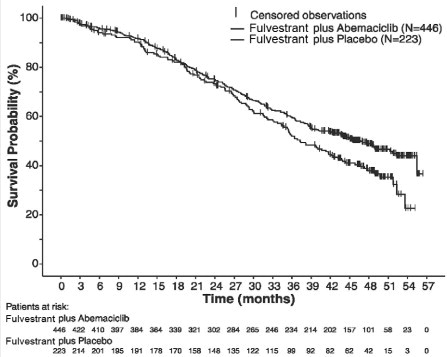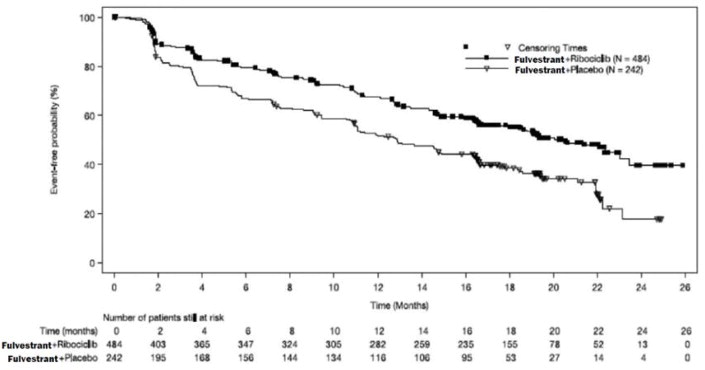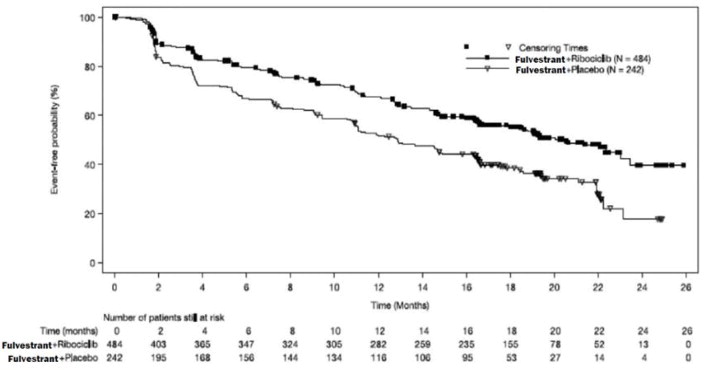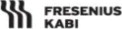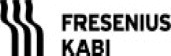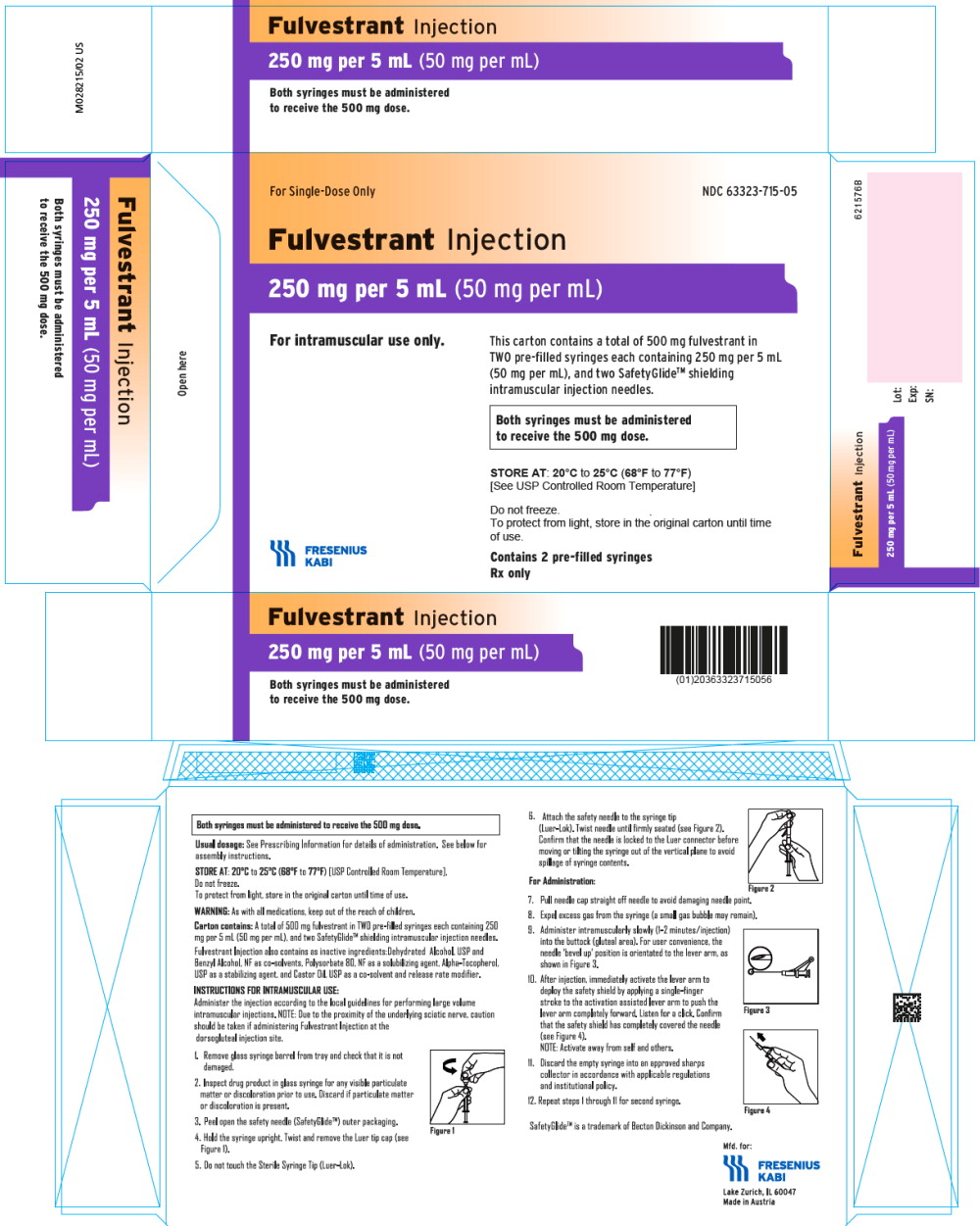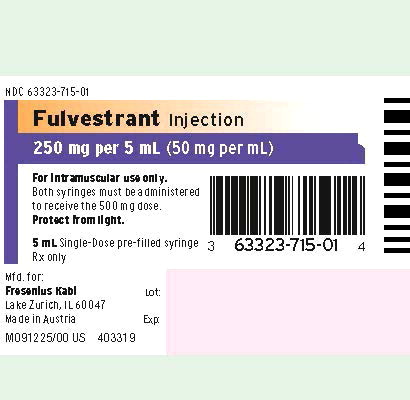 DRUG LABEL: Fulvestrant

NDC: 63323-715 | Form: INJECTION, SOLUTION
Manufacturer: Fresenius Kabi USA, LLC

Category: prescription | Type: HUMAN PRESCRIPTION DRUG LABEL
Date: 20240131

ACTIVE INGREDIENTS: Fulvestrant
 50 mg/1 mL
INACTIVE INGREDIENTS: Benzyl Alcohol; Polysorbate 80; .Alpha.-Tocopherol; Castor Oil; Alcohol

HIGHLIGHTS OF PRESCRIBING INFORMATION

These highlights do not include all the information needed to use FULVESTRANT INJECTION safely and effectively. See full prescribing information for FULVESTRANT INJECTION.
FULVESTRANT injection, for intramuscular use
Initial U.S. Approval: 2002

1 INDICATIONS AND USAGE

Fulvestrant Injection is an estrogen receptor antagonist indicated for the treatment of:

- Hormone receptor (HR)-positive, human epidermal growth factor receptor 2 (HER2)-negative advanced breast cancer in postmenopausal women not previously treated with endocrine therapy. (1)
- HR-positive advanced breast cancer in postmenopausal women with disease progression following endocrine therapy. (1)
- HR-positive, HER2-negative advanced or metastatic breast cancer in postmenopausal women in combination with ribociclib, as initial endocrine based therapy or following disease progression on endocrine therapy. (1)
- HR-positive, HER2-negative advanced or metastatic breast cancer in combination with palbociclib or abemaciclib in women with disease progression after endocrine therapy. (1)

2 DOSAGE AND ADMINISTRATION

- Fulvestrant Injection 500 mg should be administered intramuscularly into the buttocks (gluteal area) slowly (1 - 2 minutes per injection) as two 5 mL injections, one in each buttock, on Days 1, 15, 29, and once monthly thereafter. (2.1, 14)
- A dose of 250 mg is recommended in patients with moderate hepatic impairment to be administered intramuscularly into the buttock (gluteal area) slowly (1 - 2 minutes) as one 5 mL injection on Days 1, 15, 29, and once monthly thereafter. (2.2, 5.2, 8.6)

3 DOSAGE FORMS AND STRENGTHS

Fulvestrant Injection, an injection for intramuscular administration, is supplied as 250 mg/5 mL fulvestrant. (3)

4 CONTRAINDICATIONS

- Hypersensitivity. (4)

5 WARNINGS AND PRECAUTIONS

- Risk of Bleeding: Use with caution in patients with bleeding diatheses, thrombocytopenia, or anticoagulant use. (5.1)
- Increased Exposure in Patients with Hepatic Impairment: Use a 250 mg dose for patients with moderate hepatic impairment. (2.2, 5.2, 8.6)
- Injection Site Reaction: Use caution while administering Fulvestrant Injection at the dorsogluteal injection site due to the proximity of the underlying sciatic nerve. (5.3)
- Embryo-Fetal Toxicity: Can cause fetal harm. Advise females of reproductive potential of the potential risk to a fetus and to use effective contraception. (5.4, 8.1, 8.3)
- Immunoassay Measurement of Serum Estradiol: Fulvestrant Injection can interfere with estradiol measurement by immunoassay, resulting in falsely elevated estradiol levels. (5.5)

6 ADVERSE REACTIONS

- The most common adverse reactions occurring in ≥5% of patients receiving fulvestrant 500 mg were: injection site pain, nausea, bone pain, arthralgia, headache, back pain, fatigue, pain in extremity, hot flash, vomiting, anorexia, asthenia, musculoskeletal pain, cough, dyspnea, and constipation. (6.1)
- Increased hepatic enzymes (ALT, AST, ALP) occurred in >15% of fulvestrant patients and were not dose-dependent. (6.1)

To report SUSPECTED ADVERSE REACTIONS, contact Fresenius Kabi USA, LLC at 1-800-551-7176 or FDA at 1-800-FDA-1088 or www.fda.gov/medwatch.

7 DRUG INTERACTIONS

- There are no known drug-drug interactions. (7)

8 USE IN SPECIFIC POPULATIONS

- Lactation: Advise not to breastfeed. (8.2)

FULL PRESCRIBING INFORMATION

1 INDICATIONS AND USAGE

Monotherapy

Fulvestrant Injection is indicated for the treatment of:

- Hormone receptor (HR)-positive, human epidermal growth factor receptor 2 (HER2)-negative advanced breast cancer in postmenopausal women not previously treated with endocrine therapy, or
- HR-positive advanced breast cancer in postmenopausal women with disease progression following endocrine therapy.

Combination Therapy

Fulvestrant Injection is indicated for the treatment of:

- HR-positive, HER2-negative advanced or metastatic breast cancer in postmenopausal women in combination with ribociclib as initial endocrine based therapy or following disease progression on endocrine therapy.
- HR-positive, HER2-negative advanced or metastatic breast cancer in combination with palbociclib or abemaciclib in women with disease progression after endocrine therapy.

2 DOSAGE AND ADMINISTRATION

2.1 Recommended Dose

Monotherapy

The recommended dose of Fulvestrant Injection is 500 mg to be administered intramuscularly into the buttocks (gluteal area) slowly (1 - 2 minutes per injection) as two 5 mL injections, one in each buttock, on Days 1, 15, 29, and once monthly thereafter [see Clinical Studies (14)].

Combination Therapy

When Fulvestrant Injection is used in combination with palbociclib, abemaciclib, or ribociclib, the recommended dose of Fulvestrant Injection is 500 mg to be administered intramuscularly into the buttocks (gluteal area) slowly (1 - 2 minutes per injection) as two 5 mL injections, one in each buttock, on Days 1, 15, 29, and once monthly thereafter.

When Fulvestrant Injection is used in combination with palbociclib, the recommended dose of palbociclib is a 125 mg capsule taken orally once daily for 21 consecutive days followed by 7 days off treatment to comprise a complete cycle of 28 days. Palbociclib should be taken with food. Refer to the Full Prescribing Information for palbociclib.

When Fulvestrant Injection is used in combination with abemaciclib, the recommended dose of abemaciclib is 150 mg orally, twice daily. Abemaciclib may be taken with or without food. Refer to the Full Prescribing Information for abemaciclib.

When Fulvestrant Injection is used in combination with ribociclib, the recommended dose of ribociclib is 600 mg taken orally, once daily for 21 consecutive days followed by 7 days off treatment resulting in a complete cycle of 28 days. Ribociclib can be taken with or without food. Refer to the Full Prescribing Information for ribociclib.

Pre/perimenopausal women treated with the combination of Fulvestrant Injection plus palbociclib, abemaciclib, or ribociclib, should be treated with luteinizing hormone-releasing hormone (LHRH) agonists according to current clinical practice standards [see Clinical Studies (14)].

2.2 Dose Modification

Monotherapy

Hepatic Impairment:

A dose of 250 mg is recommended for patients with moderate hepatic impairment (Child-Pugh class B) to be administered intramuscularly into the buttock (gluteal area) slowly (1 - 2 minutes) as one 5 mL injection on Days 1, 15, 29, and once monthly thereafter.

Fulvestrant Injection has not been evaluated in patients with severe hepatic impairment (Child-Pugh class C) [see Warnings and Precautions (5.2) and Use in Specific Populations (8.6)].

Combination Therapy

When Fulvestrant Injection is used in combination with palbociclib, abemaciclib, or ribociclib, refer to monotherapy dose modification instructions for Fulvestrant Injection.

Refer to the Full Prescribing Information of co-administered palbociclib, abemaciclib, or ribociclib, for dose modification guidelines in the event of toxicities, for use with concomitant medications, and other relevant safety information.

2.3 Administration Technique

Administer the injection according to the local guidelines for performing large volume intramuscular injections.

NOTE: Due to the proximity of the underlying sciatic nerve, caution should be taken if administering Fulvestrant Injection at the dorsogluteal injection site [see Warnings and Precautions (5.3) and Adverse Reactions (6.1)].

The proper method of administration of Fulvestrant Injection for intramuscular use is described in the following instructions.

For each single-dose prefilled syringe:

1. Remove glass syringe barrel from tray and check that it is not damaged.
2. Inspect drug product in glass syringe for any visible particulate matter or discoloration prior to use. Discard if particulate matter or discoloration is present.
3. Peel open the safety needle (SafetyGlideTM) outer packaging.
4. Hold the syringe upright. Twist and remove the Luer tip cap (see Figure 1).
  Figure 1
5. Do Not Touch the Sterile Syringe Tip (Luer-Lok).
6. Attach the safety needle to the syringe tip (Luer-Lok). Twist needle until firmly seated (see Figure 2). Confirm that the needle is locked to the Luer connector before moving or tilting the syringe out of the vertical plane to avoid spillage of syringe contents.
  Figure 2
  For Administration:
7. Pull needle cap straight off needle to avoid damaging needle point.
8. Expel excess gas from the syringe (a small gas bubble may remain).
9. Administer intramuscularly slowly (1-2 minutes/injection) into the buttock (gluteal area). For user convenience, the needle ‘bevel up’ position is orientated to the lever arm, as shown in Figure 3.
  Figure 3
10. After injection, immediately activate the lever arm to deploy the safety shield by applying a single finger stroke to the activation assisted lever arm to push the lever arm completely forward. Listen for a click. Confirm that the safety shield has completely covered the needle (see Figure 4). NOTE: Activate away from self and others.
  Figure 4
11. Discard the empty syringe into an approved sharps collector in accordance with applicable regulations and institutional policy.
12. Repeat steps 1 through 11 for second syringe.

How To Use Fulvestrant Injection

For the 2 x 5 mL syringe package, the contents of both syringes must be injected to receive the 500 mg recommended dose.

SAFETYGLIDETM INSTRUCTIONS FROM BECTON DICKINSON

SafetyGlideTM is a trademark of Becton Dickinson and Company.

Important Administration Information

To help avoid HIV (AIDS), HBV (Hepatitis), and other infectious diseases due to accidental needlesticks, contaminated needles should not be recapped or removed, unless there is no alternative or that such action is required by a specific medical procedure. Hands must remain behind the needle at all times during use and disposal.

Do not autoclave SafetyGlideTM Needle before use.

Becton Dickinson guarantees the contents of their unopened or undamaged packages to be sterile, non-toxic, and non-pyrogenic.

3 DOSAGE FORMS AND STRENGTHS

Fulvestrant Injection, an injection for intramuscular administration, is supplied as 5-mL single-dose prefilled syringes containing 250 mg/5 mL fulvestrant.

4 CONTRAINDICATIONS

Fulvestrant Injection is contraindicated in patients with a known hypersensitivity to the drug or to any of its components. Hypersensitivity reactions, including urticaria and angioedema, have been reported in association with fulvestrant [see Adverse Reactions (6.2)].

5 WARNINGS AND PRECAUTIONS

5.1 Risk of Bleeding

Because Fulvestrant Injection is administered intramuscularly, it should be used with caution in patients with bleeding diatheses, thrombocytopenia, or anticoagulant use.

5.2 Increased Exposure in Patients with Hepatic Impairment

The safety and pharmacokinetics of fulvestrant were evaluated in a study in seven subjects with moderate hepatic impairment (Child-Pugh class B) and seven subjects with normal hepatic function.

Exposure was increased in patients with moderate hepatic impairment, therefore, a dose of 250 mg is recommended [see Dosage and Administration (2.2)].

Fulvestrant has not been studied in patients with severe hepatic impairment (Child-Pugh class C) [see Use in Specific Populations (8.6)].

5.3 Injection Site Reaction

Injection site related events including sciatica, neuralgia, neuropathic pain, and peripheral neuropathy have been reported with fulvestrant injection. Caution should be taken while administering Fulvestrant Injection at the dorsogluteal injection site due to the proximity of the underlying sciatic nerve [see Dosage and Administration (2.3) and Adverse Reactions (6.1)].

5.4 Embryo-Fetal Toxicity

Based on findings from animal studies and its mechanism of action, Fulvestrant Injection can cause fetal harm when administered to a pregnant woman. In animal reproduction studies, administration of fulvestrant to pregnant rats and rabbits during organogenesis resulted in embryo-fetal toxicity at daily doses that are significantly less than the maximum recommended human dose. Advise pregnant women of the potential risk to a fetus. Advise females of reproductive potential to use effective contraception during treatment with Fulvestrant Injection and for one year after the last dose [see Use in Specific Populations (8.1), (8.3) and Clinical Pharmacology (12.1)].

5.5 Immunoassay Measurement of Serum Estradiol

Due to structural similarity of fulvestrant and estradiol, fulvestrant can interfere with estradiol measurement by immunoassay, resulting in falsely elevated estradiol levels.

6 ADVERSE REACTIONS

The following adverse reactions are discussed in more detail in other sections of the labeling:

- Risk of Bleeding [see Warnings and Precautions (5.1)]
- Increased Exposure in Patients with Hepatic Impairment [see Warnings and Precautions (5.2)]
- Injection Site Reaction [see Warnings and Precautions (5.3)]
- Embryo-Fetal Toxicity [see Warnings and Precautions (5.4)]

6.1 Clinical Trials Experience

Because clinical trials are conducted under widely varying conditions, the adverse reaction rates observed cannot be directly compared to rates in other trials and may not reflect the rates observed in clinical practice.

Monotherapy

Comparison of Fulvestrant Injection 500 mg and Fulvestrant Injection 250 mg (CONFIRM)

The following adverse reactions (ARs) were calculated based on the safety analysis of CONFIRM comparing the administration of fulvestrant 500 mg intramuscularly once a month with fulvestrant 250 mg intramuscularly once a month. The most frequently reported adverse reactions in the fulvestrant 500 mg group were injection site pain (11.6% of patients), nausea (9.7% of patients), and bone pain (9.4% of patients); the most frequently reported adverse reactions in the fulvestrant 250 mg group were nausea (13.6% of patients), back pain (10.7% of patients), and injection site pain (9.1% of patients).

Table 1 lists adverse reactions reported with an incidence of 5% or greater, regardless of assessed causality, from CONFIRM.

Table 1: Adverse Reactions in CONFIRM (≥ 5% in Either Treatment Group)
Adverse Reactions | Fulvestrant 500 mg N=361 % | Fulvestrant 250 mg N=374 %
Body as a Whole
Injection Site Pain^1 | 12 | 9
Headache | 8 | 7
Back Pain | 8 | 11
Fatigue | 8 | 6
Pain in Extremity | 7 | 7
Asthenia | 6 | 6
Vascular System
Hot Flash | 7 | 6
Digestive System
Nausea | 10 | 14
Vomiting | 6 | 6
Anorexia | 6 | 4
Constipation | 5 | 4
Musculoskeletal System
Bone Pain | 9 | 8
Arthralgia | 8 | 8
Musculoskeletal Pain | 6 | 3
Respiratory System
Cough | 5 | 5
Dyspnea | 4 | 5
^1. Including more severe injection site related sciatica, neuralgia, neuropathic pain, and peripheral neuropathy.

In the pooled safety population (N=1127) from clinical trials comparing fulvestrant 500 mg to fulvestrant 250 mg, post-baseline increases of ≥1 CTC grade in either AST, ALT, or alkaline phosphatase were observed in >15% of patients receiving fulvestrant. Grade 3-4 increases were observed in 1-2% of patients. The incidence and severity of increased hepatic enzymes (ALT, AST, ALP) did not differ between the 250 mg and the 500 mg fulvestrant arms.

Comparison of Fulvestrant Injection 500 mg and Anastrozole 1 mg (FALCON)

The safety of fulvestrant 500 mg versus anastrozole 1 mg was evaluated in FALCON. The data described below reflect exposure to fulvestrant in 228 out of 460 patients with HR-positive advanced breast cancer in postmenopausal women not previously treated with endocrine therapy who received at least one (1) dose of treatment in FALCON.

Permanent discontinuation associated with an adverse reaction occurred in 4 of 228 (1.8%) patients receiving fulvestrant, and in 3 of 232 (1.3%) patients receiving anastrozole. Adverse reactions leading to discontinuation for those patients receiving fulvestrant included drug hypersensitivity (0.9%), injection site hypersensitivity (0.4%), and elevated liver enzymes (0.4%).

The most common adverse reactions (≥10%) of any grade reported in patients in the fulvestrant arm were arthralgia, hot flash, fatigue, and nausea.

Adverse reactions reported in patients who received fulvestrant in FALCON at an incidence of ≥5% in either treatment arm are listed in Table 2, and laboratory abnormalities are listed in Table 3.

Table 2: Adverse Reactions in FALCON
Adverse Reactions | Fulvestrant 500 mg N=228 |  | Anastrozole 1 mg N=232
Adverse Reactions | All Grades % | Grade 3 or 4 % | All Grades % | Grade 3 or 4 %
Vascular Disorders
Hot flash | 11 | 0 | 10 | 0
Gastrointestinal Disorders
Nausea | 11 | 0 | 10 | <1
Diarrhea | 6 | 0 | 6 | <1
Musculoskeletal and Connective Tissue Disorders
Arthralgia | 17 | 0 | 10 | 0
Myalgia | 7 | 0 | 3 | 0
Pain in extremity | 6 | 0 | 4 | 0
Back pain | 9 | <1 | 6 | 0
General Disorders and Administration Site Conditions
Fatigue | 11 | <1 | 7 | <1

Table 3: Laboratory Abnormalities in FALCON^1
Laboratory Parameters | Fulvestrant 500 mg N=228 |  | Anastrozole 1 mg N=232
Laboratory Parameters | All Grades % | Grade 3 or 4 % | All Grades % | Grade 3 or 4 %
Alanine aminotransferase increased (ALT) | 7 | 1 | 3 | 0
Aspartate aminotransferase increased (AST) | 5 | 1 | 3 | <1
^1. In FALCON, post-baseline increases of ≥1 CTC grade in either AST, ALT, or alkaline phosphatase were observed in >10% of patients receiving fulvestrant. Grade 3-4 increases were observed in 1%-3% of patients.

Comparison of Fulvestrant Injection 250 mg and Anastrozole 1 mg in Combined Trials (Studies 0020 and 0021)

The most commonly reported adverse reactions in the fulvestrant and anastrozole treatment groups were gastrointestinal symptoms (including nausea, vomiting, constipation, diarrhea, and abdominal pain), headache, back pain, vasodilatation (hot flashes), and pharyngitis.

Injection site reactions with mild transient pain and inflammation were seen with fulvestrant and occurred in 7% of patients given the single 5 mL injection (Study 0020) and in 27% of patients given the 2 x 2.5 mL injections (Study 0021) in the two clinical trials that compared fulvestrant 250 mg and anastrozole 1 mg.

Table 4 lists adverse reactions reported with an incidence of 5% or greater, regardless of assessed causality, from the two controlled clinical trials comparing the administration of fulvestrant 250 mg intramuscularly once a month with anastrozole 1 mg orally once a day.

Table 4: Adverse Reactions in Studies 0020 and 0021 (≥ 5% from Combined Data)
Adverse Reactions | Fulvestrant 250 mg N=423 % | Anastrozole 1 mg N=423 %
Body as a Whole | 68 | 68
Asthenia | 23 | 27
Pain | 19 | 20
Headache | 15 | 17
Back Pain | 14 | 13
Abdominal Pain | 12 | 12
Injection Site Pain^1 | 11 | 7
Pelvic Pain | 10 | 9
Chest Pain | 7 | 5
Flu Syndrome | 7 | 6
Fever | 6 | 6
Accidental Injury | 5 | 6
Cardiovascular System | 30 | 28
Vasodilatation | 18 | 17
Digestive System | 52 | 48
Nausea | 26 | 25
Vomiting | 13 | 12
Constipation | 13 | 11
Diarrhea | 12 | 13
Anorexia | 9 | 11
Hemic and Lymphatic Systems | 14 | 14
Anemia | 5 | 5
Metabolic and Nutritional Disorders | 18 | 18
Peripheral Edema | 9 | 10
Musculoskeletal System | 26 | 28
Bone Pain | 16 | 14
Arthritis | 3 | 6
Nervous System | 34 | 34
Dizziness | 7 | 7
Insomnia | 7 | 9
Paresthesia | 6 | 8
Depression | 6 | 7
Anxiety | 5 | 4
Respiratory System | 39 | 34
Pharyngitis | 16 | 12
Dyspnea | 15 | 12
Cough Increased | 10 | 10
Skin and Appendages | 22 | 23
Rash | 7 | 8
Sweating | 5 | 5
Urogenital System | 18 | 15
Urinary Tract Infection | 6 | 4
^1. Including more severe injection site related sciatica, neuralgia, neuropathic pain, and peripheral neuropathy. All patients on fulvestrant received injections, but only those anastrozole patients who were in Study 0021 received placebo injections.

Combination Therapy

Combination Therapy with Palbociclib (PALOMA-3)

The safety of fulvestrant 500 mg plus palbociclib 125 mg/day versus fulvestrant plus placebo was evaluated in PALOMA-3. The data described below reflect exposure to fulvestrant plus palbociclib in 345 out of 517 patients with HR-positive, HER2-negative advanced or metastatic breast cancer who received at least 1 dose of treatment in PALOMA-3. The median duration of treatment for fulvestrant plus palbociclib was 10.8 months while the median duration of treatment for fulvestrant plus placebo arm was 4.8 months.

No dose reduction was allowed for fulvestrant in PALOMA-3. Dose reductions of palbociclib due to an adverse reaction of any grade occurred in 36% of patients receiving fulvestrant plus palbociclib.

Permanent discontinuation associated with an adverse reaction occurred in 19 of 345 (6%) patients receiving fulvestrant plus palbociclib, and in 6 of 172 (3%) patients receiving fulvestrant plus placebo. Adverse reactions leading to discontinuation for those patients receiving fulvestrant plus palbociclib included fatigue (0.6%), infections (0.6%), and thrombocytopenia (0.6%).

The most common adverse reactions (≥10%) of any grade reported in patients in the fulvestrant plus palbociclib arm by descending frequency were neutropenia, leukopenia, infections, fatigue, nausea, anemia, stomatitis, diarrhea, thrombocytopenia, vomiting, alopecia, rash, decreased appetite, and pyrexia.

The most frequently reported Grade ≥3 adverse reactions (≥5%) in patients receiving fulvestrant plus palbociclib in descending frequency were neutropenia and leukopenia.

Adverse reactions (≥10%) reported in patients who received fulvestrant plus palbociclib or fulvestrant plus placebo in PALOMA-3 are listed in Table 5, and laboratory abnormalities are listed in Table 6.

Table 5: Adverse Reactions (≥10%) in PALOMA-3
Adverse Reaction | Fulvestrant plus Palbociclib N=345 |  |  | Fulvestrant plus Placebo N=172
Adverse Reaction | All Grades % | Grade 3 % | Grade 4 % | All Grades % | Grade 3 % | Grade 4 %
Infections and Infestations
Infections^1 | 47^2 | 3 | 1 | 31 | 3 | 0
Blood and Lymphatic System Disorders
Neutropenia | 83 | 55 | 11 | 4 | 1 | 0
Leukopenia | 53 | 30 | 1 | 5 | 1 | 1
Anemia | 30 | 4 | 0 | 13 | 2 | 0
Thrombocytopenia | 23 | 2 | 1 | 0 | 0 | 0
Metabolism and Nutrition Disorders
Decreased appetite | 16 | 1 | 0 | 8 | 1 | 0
Gastrointestinal Disorders
Nausea | 34 | 0 | 0 | 28 | 1 | 0
Stomatitis^3 | 28 | 1 | 0 | 13 | 0 | 0
Diarrhea | 24 | 0 | 0 | 19 | 1 | 0
Vomiting | 19 | 1 | 0 | 15 | 1 | 0
Skin and Subcutaneous Tissue Disorders
Alopecia | 18^4 | N/A | N/A | 6^5 | N/A | N/A
Rash^6 | 17 | 1 | 0 | 6 | 0 | 0
General Disorders and Administration Site Conditions
Fatigue | 41 | 2 | 0 | 29 | 1 | 0
Pyrexia | 13 | <1 | 0 | 5 | 0 | 0
Grading according to CTCAE v.4.0.
CTCAE=Common Terminology Criteria for Adverse Events; N=number of patients; N/A=not applicable.
^1. Infections includes all reported preferred terms (PTs) that are part of the System Organ Class Infections and infestations.
^2. Most common infections (≥1%) include: nasopharyngitis, upper respiratory infection, urinary tract infection, influenza, bronchitis, rhinitis, conjunctivitis, pneumonia, sinusitis, cystitis, oral herpes, respiratory tract infection, gastroenteritis, tooth infection, pharyngitis, eye infection, herpes simplex, and paronychia.
^3. Stomatitis includes: aphthous stomatitis, cheilitis, glossitis, glossodynia, mouth ulceration, mucosal inflammation, oral pain, oropharyngeal discomfort, oropharyngeal pain, stomatitis.
^4. Grade 1 events - 17%; Grade 2 events - 1%.
^5. Grade 1 events - 6%.
^6. Rash includes: rash, rash maculo-papular, rash pruritic, rash erythematous, rash papular, dermatitis, dermatitis acneiform, toxic skin eruption.

Additional adverse reactions occurring at an overall incidence of <10.0% of patients receiving fulvestrant plus palbociclib in PALOMA-3 included asthenia (7.5%), aspartate aminotransferase increased (7.5%), dysgeusia (6.7%), epistaxis (6.7%), lacrimation increased (6.4%), dry skin (6.1%), alanine aminotransferase increased (5.8%), vision blurred (5.8%), dry eye (3.8%), and febrile neutropenia (0.9%).

Table 6: Laboratory Abnormalities in PALOMA-3
Laboratory Parameters | Fulvestrant plus Palbociclib N=345 |  |  | Fulvestrant plus Placebo N=172
Laboratory Parameters | All Grades % | Grade 3 % | Grade 4 % | All Grades % | Grade 3 % | Grade 4 %
WBC decreased | 99 | 45 | 1 | 26 | 0 | 1
Neutrophils decreased | 96 | 56 | 11 | 14 | 0 | 1
Anemia | 78 | 3 | 0 | 40 | 2 | 0
Platelets decreased | 62 | 2 | 1 | 10 | 0 | 0
Aspartate aminotransferase increased | 43 | 4 | 0 | 48 | 4 | 0
Alanine aminotransferase increased | 36 | 2 | 0 | 34 | 0 | 0
N=number of patients; WBC=white blood cells.

Combination Therapy with Abemaciclib (MONARCH 2)

The safety of fulvestrant (500 mg) plus abemaciclib (150 mg twice daily) versus fulvestrant plus placebo was evaluated in MONARCH 2. The data described below reflect exposure to fulvestrant in 664 patients with HR-positive, HER2-negative advanced breast cancer who received at least one dose of fulvestrant plus abemaciclib or placebo in MONARCH 2.

Median duration of treatment was 12 months for patients receiving fulvestrant plus abemaciclib and 8 months for patients receiving fulvestrant plus placebo.

Dose reductions due to an adverse reaction occurred in 43% of patients receiving fulvestrant plus abemaciclib. Adverse reactions leading to dose reductions ≥5% of patients were diarrhea and neutropenia. Abemaciclib dose reduction due to diarrhea of any grade occurred in 19% of patients receiving fulvestrant plus abemaciclib compared to 0.4% of patients receiving fulvestrant plus placebo. Abemaciclib dose reductions due to neutropenia of any grade occurred in 10% of patients receiving fulvestrant plus abemaciclib compared to no patients receiving fulvestrant plus placebo.

Permanent study treatment discontinuation due to an adverse event was reported in 9% of patients receiving fulvestrant plus abemaciclib and in 3% of patients receiving fulvestrant plus placebo. Adverse reactions leading to permanent discontinuation for patients receiving fulvestrant plus abemaciclib were infection (2%), diarrhea (1%), hepatotoxicity (1%), fatigue (0.7%), nausea (0.2%), abdominal pain (0.2%), acute kidney injury (0.2%), and cerebral infarction (0.2%).

Deaths during treatment or during the 30-day follow up, regardless of causality, were reported in 18 cases (4%) of fulvestrant plus abemaciclib treated patients versus 10 cases (5%) of fulvestrant plus placebo treated patients. Causes of death for patients receiving fulvestrant plus abemaciclib included:

7 (2%) patient deaths due to underlying disease, 4 (0.9%) due to sepsis, 2 (0.5%) due to pneumonitis, 2 (0.5%) due to hepatotoxicity, and one (0.2%) due to cerebral infarction.

The most common adverse reactions reported (≥20%) in the fulvestrant plus abemaciclib arm were diarrhea, fatigue, neutropenia, nausea, infections, abdominal pain, anemia, leukopenia, decreased appetite, vomiting, and headache (Table 7). The most frequently reported (≥5%) Grade 3 or 4 adverse reactions were neutropenia, diarrhea, leukopenia, anemia, and infections.

Table 7: Adverse Reactions ≥10% of Patients Receiving Fulvestrant Plus Abemaciclib and ≥2% Higher Than Fulvestrant Plus Placebo in MONARCH 2
Adverse Reactions | Fulvestrant plus Abemaciclib N=441 |  |  | Fulvestrant plus Placebo N=223
Adverse Reactions | All Grades % | Grade 3 % | Grade 4 % | All Grades % | Grade 3 % | Grade 4 %
Gastrointestinal Disorders
Diarrhea | 86 | 13 | 0 | 25 | <1 | 0
Nausea | 45 | 3 | 0 | 23 | 1 | 0
Abdominal pain^1 | 35 | 2 | 0 | 16 | 1 | 0
Vomiting | 26 | <1 | 0 | 10 | 2 | 0
Stomatitis | 15 | <1 | 0 | 10 | 0 | 0
Infections and Infestations
Infections^2 | 43 | 5 | <1 | 25 | 3 | <1
Blood and Lymphatic System Disorders
Neutropenia^3 | 46 | 24 | 3 | 4 | 1 | <1
Anemia^4 | 29 | 7 | <1 | 4 | 1 | 0
Leukopenia^5 | 28 | 9 | <1 | 2 | 0 | 0
Thrombocytopenia^6 | 16 | 2 | 1 | 3 | 0 | <1
General Disorders and Administration Site Conditions
Fatigue^7 | 46 | 3 | 0 | 32 | <1 | 0
Edema peripheral | 12 | 0 | 0 | 7 | 0 | 0
Pyrexia | 11 | <1 | <1 | 6 | <1 | 0
Metabolism and Nutrition Disorders
Decreased appetite | 27 | 1 | 0 | 12 | <1 | 0
Respiratory, Thoracic and Mediastinal Disorders
Cough | 13 | 0 | 0 | 11 | 0 | 0
Skin and Subcutaneous Tissue Disorders
Alopecia | 16 | 0 | 0 | 2 | 0 | 0
Pruritus | 13 | 0 | 0 | 6 | 0 | 0
Rash | 11 | 1 | 0 | 4 | 0 | 0
Nervous System Disorders
Headache | 20 | 1 | 0 | 15 | <1 | 0
Dysgeusia | 18 | 0 | 0 | 3 | 0 | 0
Dizziness | 12 | 1 | 0 | 6 | 0 | 0
Investigations
Alanine aminotransferase increased | 13 | 4 | <1 | 5 | 2 | 0
Aspartate aminotransferase increased | 12 | 2 | 0 | 7 | 3 | 0
Creatinine increased | 12 | <1 | 0 | <1 | 0 | 0
Weight decreased | 10 | <1 | 0 | 2 | <1 | 0
^1. Includes abdominal pain, abdominal pain upper, abdominal pain lower, abdominal discomfort, abdominal tenderness.
^2. Includes upper respiratory tract infection, urinary tract infection, lung infection, pharyngitis, conjunctivitis, sinusitis, vaginal infection, sepsis.
^3. Includes neutropenia, neutrophil count decreased.
^4. Includes anemia, hematocrit decreased, hemoglobin decreased, red blood cell count decreased.
^5. Includes leukopenia, white blood cell count decreased.
^6. Includes platelet count decreased, thrombocytopenia. ^7. Includes asthenia, fatigue.

Additional adverse reactions in MONARCH 2 include venous thromboembolic events (deep vein thrombosis, pulmonary embolism, cerebral venous sinus thrombosis, subclavian vein thrombosis, axillary vein thrombosis, and DVT inferior vena cava), which were reported in 5% of patients treated with fulvestrant plus abemaciclib as compared to 0.9% of patients treated with fulvestrant plus placebo.

Table 8: Laboratory Abnormalities ≥10% in Patients Receiving Fulvestrant Plus Abemaciclib and ≥2% Higher Than Fulvestrant Plus Placebo in MONARCH 2
Laboratory Parameters | Fulvestrant plus Abemaciclib N=441 |  |  | Fulvestrant plus Placebo N=223
Laboratory Parameters | All Grades % | Grade 3 % | Grade 4 % | All Grades % | Grade 3 % | Grade 4 %
Creatinine increased | 98 | 1 | 0 | 74 | 0 | 0
White blood cell decreased | 90 | 23 | <1 | 33 | <1 | 0
Neutrophil count decreased | 87 | 29 | 4 | 30 | 4 | <1
Anemia | 84 | 3 | 0 | 33 | <1 | 0
Lymphocyte count decreased | 63 | 12 | <1 | 32 | 2 | 0
Platelet count decreased | 53 | <1 | 1 | 15 | 0 | 0
Alanine aminotransferase increased | 41 | 4 | <1 | 32 | 1 | 0
Aspartate aminotransferase increased | 37 | 4 | 0 | 25 | 4 | <1

Combination Therapy with Ribociclib (MONALEESA-3)

The safety of fulvestrant 500 mg plus ribociclib 600 mg versus fulvestrant plus placebo was evaluated in MONALEESA-3. The data described below reflect exposure to fulvestrant plus ribociclib in 483 out of 724 postmenopausal patients with HR-positive, HER2-negative advanced or metastatic breast cancer for initial endocrine based therapy or after disease progression on endocrine therapy who received at least one dose of fulvestrant plus ribociclib or placebo in MONALEESA-3. Median duration of treatment was 15.8 months for fulvestrant plus ribociclib and 12 months for Fulvestrant plus placebo.

Dose reductions due to adverse reactions occurred in 32% of patients receiving fulvestrant plus ribociclib and in 3% of patients receiving fulvestrant plus placebo. Among patients receiving fulvestrant plus ribociclib, 8% were reported to have permanently discontinued both fulvestrant plus ribociclib, and 9% were reported to have discontinued ribociclib alone due to ARs. Among patients receiving fulvestrant plus placebo, 4% were reported to have permanently discontinued both fulvestrant and placebo and 2% were reported to have discontinued placebo alone due to ARs.

Adverse reactions leading to treatment discontinuation of fulvestrant plus ribociclib (as compared to fulvestrant plus placebo) were ALT increased (5% vs. 0%), AST increased (3% vs. 0.6%), and vomiting (1% vs. 0%).

The most common adverse reactions (reported at a frequency ≥20% on the fulvestrant plus ribociclib arm and ≥2% higher than fulvestrant plus placebo) were neutropenia, infections, leukopenia, cough, nausea, diarrhea, vomiting, constipation, pruritus, and rash. The most frequently reported Grade 3/4 adverse reactions (reported at a frequency ≥5%) in patients receiving fulvestrant plus ribociclib in descending frequency were neutropenia, leukopenia, infections, and abnormal liver function tests.

Adverse reactions and laboratory abnormalities occurring in patients in MONALEESA-3 are listed in Table 9 and Table 10, respectively.

Table 9: Adverse Reactions Occurring in ≥10% and ≥2% higher than Fulvestrant Injection plus Placebo Arm in MONALEESA-3 (All Grades)
Adverse Reactions | Fulvestrant plus Ribociclib N=483 |  |  | Fulvestrant plus Placebo N=241
Adverse Reactions | All Grades % | Grade 3 % | Grade 4 % | All Grades % | Grade 3 % | Grade 4 %
Infections and Infestations
Infections^1 | 42 | 5 | 0 | 30 | 2 | 0
Blood and Lymphatic System Disorders
Neutropenia | 69 | 46 | 7 | 2 | 0 | 0
Leukopenia | 27 | 12 | <1 | <1 | 0 | 0
Anemia | 17 | 3 | 0 | 5 | 2 | 0
Metabolism and Nutrition Disorders
Decreased appetite | 16 | <1 | 0 | 13 | 0 | 0
Nervous System Disorders
Dizziness | 13 | <1 | 0 | 8 | 0 | 0
Respiratory, Thoracic and Mediastinal Disorders
Cough | 22 | 0 | 0 | 15 | 0 | 0
Dyspnea | 15 | 1 | <1 | 12 | 2 | 0
Gastrointestinal Disorders
Nausea | 45 | 1 | 0 | 28 | <1 | 0
Diarrhea | 29 | <1 | 0 | 20 | <1 | 0
Vomiting | 27 | 1 | 0 | 13 | 0 | 0
Constipation | 25 | <1 | 0 | 12 | 0 | 0
Abdominal pain | 17 | 1 | 0 | 13 | <1 | 0
Skin and Subcutaneous Tissue Disorders
Alopecia | 19 | 0 | 0 | 5 | 0 | 0
Pruritus | 20 | <1 | 0 | 7 | 0 | 0
Rash | 23 | <1 | 0 | 7 | 0 | 0
General Disorders and Administration Site Conditions
Edema peripheral | 15 | 0 | 0 | 7 | 0 | 0
Pyrexia | 11 | <1 | 0 | 7 | 0 | 0
Investigations
Alanine aminotransferase increased | 15 | 7 | 2 | 5 | <1 | 0
Aspartate aminotransferase increased | 13 | 5 | 1 | 5 | <1 | 0
Grading according to CTCAE 4.03.
CTCAE=Common Terminology Criteria for Adverse Events; N=number of patients
^1. Infections; urinary tract infections; respiratory tract infections; gastroenteritis; sepsis (<1%).
Additional adverse reactions in MONALEESA-3 for patients receiving fulvestrant plus ribociclib included asthenia (14%), dyspepsia (10%), thrombocytopenia (9%), dry skin (8%), dysgeusia (7%), electrocardiogram QT prolonged (6%), dry mouth (5%), vertigo (5%), dry eye (5%), lacrimation increased (4%), erythema (4%), hypocalcemia (4%), blood bilirubin increased (1%), and syncope (1%).

Table 10: Laboratory Abnormalities Occurring in ≥10% of Patients in MONALEESA-3
Laboratory Parameters | Fulvestrant plus Ribociclib N=483 |  |  | Fulvestrant plus Placebo N=241
Laboratory Parameters | All Grades % | Grade 3 % | Grade 4 % | All Grades % | Grade 3 % | Grade 4 %
Hematology
Leukocyte count decreased | 95 | 25 | <1 | 26 | <1 | 0
Neutrophil count decreased | 92 | 46 | 7 | 21 | <1 | 0
Hemoglobin decreased | 60 | 4 | 0 | 35 | 3 | 0
Lymphocyte count decreased | 69 | 14 | 1 | 35 | 4 | <1
Platelet count decreased | 33 | <1 | 1 | 11 | 0 | 0
Chemistry
Creatinine increased | 65 | <1 | <1 | 33 | <1 | 0
Gamma-glutamyl transferase increased | 52 | 6 | 1 | 49 | 8 | 2
Aspartate aminotransferase increased | 49 | 5 | 2 | 43 | 3 | 0
Alanine aminotransferase increased | 44 | 8 | 3 | 37 | 2 | 0
Glucose serum decreased | 23 | 0 | 0 | 18 | 0 | 0
Phosphorous decreased | 18 | 5 | 0 | 8 | <1 | 0
Albumin decreased | 12 | 0 | 0 | 8 | 0 | 0

6.2 Postmarketing Experience

The following adverse reactions have been identified during post-approval use of fulvestrant. Because these reactions are reported voluntarily from a population of uncertain size, it is not always possible to reliably estimate their frequency or establish a causal relationship to drug exposure.

For fulvestrant 250 mg, other adverse reactions reported as drug-related and seen infrequently (<1%) include thromboembolic phenomena, myalgia, vertigo, leukopenia, and hypersensitivity reactions including angioedema and urticaria.

Vaginal bleeding has been reported infrequently (<1%), mainly in patients during the first 6 weeks after changing from existing hormonal therapy to treatment with fulvestrant. If bleeding persists, further evaluation should be considered.

Elevation of bilirubin, elevation of gamma GT, hepatitis, and liver failure have been reported infrequently (<1%).

7 DRUG INTERACTIONS

There are no known drug-drug interactions. Although, fulvestrant is metabolized by CYP 3A4 in vitro, drug interactions studies with ketoconazole or rifampin did not alter fulvestrant pharmacokinetics. Dose adjustment is not needed in patients co-prescribed CYP 3A4 inhibitors or inducers [see Clinical Pharmacology (12.3)].

8 USE IN SPECIFIC POPULATIONS

8.1 Pregnancy

Risk Summary

Based on findings from animal studies and its mechanism of action, Fulvestrant Injection can cause fetal harm when administered to a pregnant woman [see Clinical Pharmacology (12.1)]. There are no available data in pregnant women to inform the drug-associated risk. In animal reproduction studies, administration of fulvestrant to pregnant rats and rabbits during organogenesis caused embryo-fetal toxicity, including skeletal malformations and fetal loss, at daily doses that were 6% and 30% of the maximum recommended human dose based on mg/m^2, respectively [see Data]. Advise pregnant women of the potential risk to a fetus.

The estimated background risk of major birth defects and miscarriage for the indicated population is unknown. In the U.S. general population, the estimated background risk of major birth defects and miscarriage in clinically recognized pregnancies is 2-4% and 15-20%, respectively.

Data

Animal Data

Administration of fulvestrant to rats prior to and up to implantation caused embryonic loss at daily doses that were 0.6% of the daily maximum recommended human dose based on mg/m^2. When fulvestrant was administered to pregnant rats during the period of organogenesis, intramuscular doses ≥ 0.1 mg/kg/day (6% of the human recommended dose based on mg/m^2) caused effects on embryo-fetal development consistent with its antiestrogenic activity. Fulvestrant caused an increased incidence of fetal abnormalities in rats (tarsal flexure of the hind paw at 2 mg/kg/day; equivalent to the human dose based on mg/m^2) and non-ossification of the odontoid and ventral tubercle of the first cervical vertebra at doses ≥ 0.1 mg/kg/day. Fulvestrant administered at 2 mg/kg/day caused fetal loss.

When administered to pregnant rabbits during the period of organogenesis, fulvestrant caused pregnancy loss at an intramuscular dose of 1 mg/kg/day (equivalent to the human dose based on mg/m^2). Further, at 0.25 mg/kg/day (30% the human dose based on mg/m^2), fulvestrant caused increases in placental weight and post-implantation loss in rabbits. Fulvestrant was associated with an increased incidence of fetal variations in rabbits (backwards displacement of the pelvic girdle, and 27 pre-sacral vertebrae at 0.25 mg/kg/day; 30% the human dose based on mg/m^2) when administered during the period of organogenesis.

8.2 Lactation

Risk Summary

There is no information regarding the presence of fulvestrant in human milk, nor of its effects on milk production or breastfed infant. Fulvestrant can be detected in rat milk [see Data]. Because of the potential for serious adverse reactions in breastfed infants from Fulvestrant Injection, advise a lactating woman not to breastfeed during treatment with Fulvestrant Injection and for one year after the last dose.

Data

Levels of fulvestrant were approximately 12-fold higher in milk than in plasma after exposure of lactating rats to a dose of 2 mg/kg. Drug exposure in rodent pups from fulvestrant-treated lactating dams was estimated as 10% of the administered dose. In a study in rats of fulvestrant at 10 mg/kg given twice or 15 mg/kg given once (less than the recommended human dose based on mg/m^2) during lactation, offspring survival was slightly reduced.

8.3 Females and Males of Reproductive Potential

Pregnancy Testing

Pregnancy testing is recommended for females of reproductive potential within seven days prior to initiating Fulvestrant Injection.

Contraception

Females

Fulvestrant Injection can cause fetal harm when administered to a pregnant woman [see Use in Specific Populations (8.1)]. Advise females of reproductive potential to use effective contraception during treatment and for one year after the last dose.

Infertility

Based on animal studies, Fulvestrant Injection may impair fertility in females and males of reproductive potential. The effects of fulvestrant on fertility were reversible in female rats [see Nonclinical Toxicology (13.1)].

8.4 Pediatric Use

Safety and effectiveness in pediatric patients have not been established. A multi-center, single-arm, open-label, study of fulvestrant was conducted in 30 girls with McCune-Albright Syndrome (MAS) associated with Progressive Precocious Puberty (PPP). The median age at informed consent was 6 years old (range: 1 to 8).

The first 10 patients initially received fulvestrant 2 mg/kg. Based on PK data from the first 6 patients, all 10 patients receiving 2 mg/kg were escalated to a dose of 4 mg/kg and all other patients received 4 mg/kg from study entry.

Baseline measurements for vaginal bleeding days, bone age, growth velocity, and Tanner staging for at least 6 months prior to study entry were provided retrospectively by the parent, guardian, or local consultant. All measurements during the study period were collected prospectively. Patients' baseline characteristics included the following: a mean ± SD chronological age of 5.9 ± 1.8 years; a mean rate of bone age advancement (change in bone age in years divided by change in chronological age in years) of 2.0 ± 1.03; and a mean growth velocity z-score of 2.4 ± 3.26.

Twenty-nine of 30 patients completed the 12-month study period. The following results were observed: 35% (95% CI: 16%, 57%) of the 23 patients with baseline vaginal bleeding experienced a complete cessation of vaginal bleeding on-treatment (month 0 to 12); a reduction in the rate of bone age advancement during the 12-month study period compared to baseline (mean change=-0.9 [95% CI: -1.4, -0.4]); and a reduction in mean growth velocity Z-score on-treatment compared to baseline (mean change=-1.1 [95% CI: -2.7, 0.4]). There were no clinically meaningful changes in median Tanner stage (breast or pubic), mean uterine volume, or mean ovarian volume, or predicted adult height (PAH) on-treatment compared to baseline. The effect of fulvestrant on bone mineral density in children has not been studied and is not known.

Eight patients (27%) experienced adverse reactions that were considered possibly related to fulvestrant. These included injection site reactions (inflammation, pain, hematoma, pruritus, rash), abdominal pain, contusion, tachycardia, hot flash, extremity pain, and vomiting. Nine (30%) patients reported an SAE, none of which were considered related to fulvestrant. No patients discontinued study treatment due to an AE and no patients died.

Pharmacokinetics

The pharmacokinetics of fulvestrant was characterized using a population pharmacokinetic analysis with sparse samples per patient obtained from 30 female pediatric patients aged 1 to 8 years with PPP associated with MAS. Pharmacokinetic data from 294 postmenopausal women with breast cancer who received 125 or 250 mg monthly dosing regimen were also included in the analysis.

In these pediatric patients receiving 4 mg/kg monthly intramuscular dose of fulvestrant, the geometric mean (SD) CL/F was 444 (165) mL/min which was 32% lower than adults. The geometric mean (SD) steady state trough concentration (Cmin,ss) and AUCss was 4.19 (0.87) ng/mL and 3680 (1020) ng*hr/mL, respectively.

8.5 Geriatric Use

For fulvestrant 250 mg, when tumor response was considered by age, objective responses were seen in 22% and 24% of patients under 65 years of age and in 11% and 16% of patients 65 years of age and older, who were treated with fulvestrant in Study 0021 and Study 0020, respectively.

8.6 Hepatic Impairment

Fulvestrant is metabolized primarily in the liver.

The pharmacokinetics of fulvestrant were evaluated after a single dose of 100 mg in subjects with mild and moderate hepatic impairment and normal hepatic function (n=7 subjects/group), using a shorter- acting intramuscular injection formulation. Subjects with mild hepatic impairment (Child-Pugh class A) had comparable mean AUC and clearance values to those with normal hepatic function. In subjects with moderate hepatic impairment (Child-Pugh class B), the average AUC of fulvestrant increased by 70% compared to patients with normal hepatic function. AUC was positively correlated with total bilirubin concentration (p=0.012). Fulvestrant has not been studied in patients with severe hepatic impairment (Child-Pugh class C).

A dose of Fulvestrant Injection 250 mg is recommended in patients with moderate hepatic impairment (Child-Pugh class B) [see Dosage and Administration (2.2) and Warnings and Precautions (5.2)].

8.7 Renal Impairment

Negligible amounts of fulvestrant are eliminated in urine; therefore, a study in patients with renal impairment was not conducted. In the advanced breast cancer trials, fulvestrant concentrations in women with estimated creatinine clearance as low as 30 mL/min were similar to women with normal creatinine.

10 OVERDOSAGE

Human experience of overdose with fulvestrant is limited. There are isolated reports of overdose with fulvestrant in humans. No adverse reactions were seen in healthy male and female volunteers who received intravenous fulvestrant, which resulted in peak plasma concentrations at the end of the infusion, that were approximately 10 to 15 times those seen after intramuscular injection. The potential toxicity of fulvestrant at these or higher concentrations in cancer patients who may have additional comorbidities is unknown. There is no specific treatment in the event of fulvestrant overdose, and symptoms of overdose are not established. In the event of an overdose, healthcare practitioners should follow general supportive measures and should treat symptomatically.

11 DESCRIPTION

Fulvestrant Injection for intramuscular administration is an estrogen receptor antagonist. The chemical name is 7-alpha-[9-(4,4,5,5,5-penta fluoropentylsulphinyl) nonyl]estra-1,3,5-(10)- triene-3,17-beta-diol.

The molecular formula is C32H47F5O3S and its structural formula is:

Fulvestrant is a white powder with a molecular weight of 606.77. The solution for injection is a clear, colorless to yellow, viscous liquid.

Each injection contains 250 mg fulvestrant in a solution composed of 10% w/v Dehydrated Alcohol, USP and 10% w/v Benzyl Alcohol, NF, as co-solvents, 0.12% w/v Polysorbate 80, NF as a solubilizing agent, 0.06% w/v alpha-Tocopherol, USP as a stabilizing agent, and made up to 100% w/v with Castor Oil, USP as a co-solvent and release rate modifier.

12 CLINICAL PHARMACOLOGY

12.1 Mechanism of Action

Many breast cancers have estrogen receptors (ER) and the growth of these tumors can be stimulated by estrogen. Fulvestrant is an estrogen receptor antagonist that binds to the estrogen receptor in a competitive manner with affinity comparable to that of estradiol and downregulates the ER protein in human breast cancer cells.

In vitro studies demonstrated that fulvestrant is a reversible inhibitor of the growth of tamoxifen-resistant, as well as estrogen-sensitive human breast cancer (MCF-7) cell lines. In in vivo tumor studies, fulvestrant delayed the establishment of tumors from xenografts of human breast cancer MCF-7 cells in nude mice. Fulvestrant inhibited the growth of established MCF-7 xenografts and of tamoxifen-resistant breast tumor xenografts.

Fulvestrant showed no agonist-type effects in in vivo uterotrophic assays in immature or ovariectomized mice and rats. In in vivo studies in immature rats and ovariectomized monkeys, fulvestrant blocked the uterotrophic action of estradiol. In postmenopausal women, the absence of changes in plasma concentrations of FSH and LH in response to fulvestrant treatment (250 mg monthly) suggests no peripheral steroidal effects.

12.2 Pharmacodynamics

In a clinical study in postmenopausal women with primary breast cancer treated with single doses of fulvestrant 15-22 days prior to surgery, there was evidence of increasing down-regulation of ER with increasing dose. This was associated with a dose-related decrease in the expression of the progesterone receptor, an estrogen-regulated protein. These effects on the ER pathway were also associated with a decrease in Ki67 labeling index, a marker of cell proliferation.

12.3 Pharmacokinetics

Absorption:

The single dose and multiple dose PK parameters for the 500 mg dosing regimen with an additional dose (AD) at Day 15 are reported in Table 11. The additional dose of Fulvestrant Injection given two weeks after the initial dose allows for steady state concentrations to be reached within the first month of dosing.

Table 11: Summary of Fulvestrant Pharmacokinetic Parameters [gMean (CV%)] in Postmenopausal Advanced Breast Cancer Patients after Intramuscular Administration 500 mg + AD Dosing Regimen
 |  | Cmax (ng/mL) | Cmin (ng/mL) | AUC (ng.hr/mL)
500 mg + AD^1 | Single dose | 25.1 (35.3) | 16.3 (25.9) | 11400 (33.4)
500 mg + AD^1 | Multiple dose steady state^2 | 28.0 (27.9) | 12.2 (21.7) | 13100 (23.4)
^1. Additional 500 mg dose given on Day 15
^2. Month 3

Distribution:

The apparent volume of distribution at steady state is approximately 3 to 5 L/kg. This suggests that distribution is largely extravascular. Fulvestrant is highly (99%) bound to plasma proteins; VLDL, LDL, and HDL lipoprotein fractions appear to be the major binding components. The role of sex hormone- binding globulin, if any, could not be determined.

Metabolism:

Biotransformation and disposition of fulvestrant in humans have been determined following intramuscular and intravenous administration of ^14C-labeled fulvestrant. Metabolism of fulvestrant appears to involve combinations of a number of possible biotransformation pathways analogous to those of endogenous steroids, including oxidation, aromatic hydroxylation, conjugation with glucuronic acid and/or sulphate at the 2, 3, and 17 positions of the steroid nucleus, and oxidation of the side chain sulphoxide. Identified metabolites are either less active or exhibit similar activity to fulvestrant in antiestrogen models.

Studies using human liver preparations and recombinant human enzymes indicate that cytochrome P-450 3A4 (CYP 3A4) is the only P-450 isoenzyme involved in the oxidation of fulvestrant; however, the relative contribution of P-450 and non-P-450 routes in vivo is unknown.

Excretion:

Fulvestrant was rapidly cleared by the hepatobiliary route with excretion primarily via the feces (approximately 90%). Renal elimination was negligible (less than 1%). After an intramuscular injection of 250 mg, the clearance (Mean ± SD) was 690 ± 226 mL/min with an apparent half-life about 40 days.

Special Populations:

Geriatric:

In patients with breast cancer, there was no difference in fulvestrant pharmacokinetic profile related to age (range 33 to 89 years).

Gender:

Following administration of a single intravenous dose, there were no pharmacokinetic differences between men and women or between premenopausal and postmenopausal women. Similarly, there were no differences between men and postmenopausal women after intramuscular administration.

Race:

In the advanced breast cancer treatment trials, the potential for pharmacokinetic differences due to race have been evaluated in 294 women including 87.4% Caucasian, 7.8% Black, and 4.4% Hispanic. No differences in fulvestrant plasma pharmacokinetics were observed among these groups. In a separate trial, pharmacokinetic data from postmenopausal ethnic Japanese women were similar to those obtained in non-Japanese patients.

Drug-Drug Interactions:

There are no known drug-drug interactions. Fulvestrant does not significantly inhibit any of the major CYP isoenzymes, including CYP 1A2, 2C9, 2C19, 2D6, and 3A4 in vitro, and studies of co- administration of fulvestrant with midazolam indicate that therapeutic doses of fulvestrant have no inhibitory effects on CYP 3A4 or alter blood levels of drug metabolized by that enzyme. Although fulvestrant is partly metabolized by CYP 3A4, a clinical study with rifampin, an inducer of CYP 3A4, showed no effect on the pharmacokinetics of fulvestrant. Also, results from a healthy volunteer study with ketoconazole, a potent inhibitor of CYP 3A4, indicated that ketoconazole had no effect on the pharmacokinetics of fulvestrant and dosage adjustment is not necessary in patients co-prescribed CYP 3A4 inhibitors or inducers [see Drug Interactions (7)]. Data from a clinical trial in patients with breast cancer showed that there was no clinically relevant drug interaction when fulvestrant is co-administered with palbociclib, abemaciclib, or ribociclib.

13 NONCLINICAL TOXICOLOGY

13.1 Carcinogenesis, Mutagenesis, Impairment of Fertility

Two-year carcinogenesis studies were conducted in rats and mice. Positive findings were observed in both species. Rats were treated at intramuscular doses of 15 mg/kg/30 days, 10 mg/rat/30 days, and 10 mg/rat/15 days.

These doses correspond to 0.9-, 1.5-, and 3-fold (in females) and 0.8-, 0.8-, and 2-fold (in males) the systemic exposure [AUC0-30 days] achieved in women receiving the recommended dose of 500 mg/month. An increased incidence of benign ovarian granulosa cell tumors and testicular Leydig cell tumors was evident, in females dosed at 10 mg/rat/15 days and males dosed at 15 mg/rat/30 days, respectively. Mice were treated at oral doses of 0, 20, 150, and 500 mg/kg/day. These doses correspond to 0-, 0.8-, 8.4-, and 18-fold (in females) and 0.8-, 7.1-, and 11.9-fold (in males), the systemic exposure (AUC0-30 days) achieved in women receiving the recommended dose of 500 mg/month. There was an increased incidence of sex cord stromal tumors (both benign and malignant) in the ovary of mice at doses of 150 and 500 mg/kg/day. Induction of such tumors is consistent with the pharmacology-related endocrine feedback alterations in gonadotropin levels caused by an antiestrogen.

Fulvestrant was not mutagenic or clastogenic in multiple in vitro tests with and without the addition of a mammalian liver metabolic activation factor (bacterial mutation assay in strains of Salmonella typhimurium and Escherichia coli, in vitro cytogenetics study in human lymphocytes, mammalian cell mutation assay in mouse lymphoma cells, and in vivo micronucleus test in rat).

In female rats, fulvestrant administered at doses ≥0.01 mg/kg/day (0.6% the human recommended dose based on body surface area [BSA in mg/m^2]), for 2 weeks prior to and for 1 week following mating, caused a reduction in fertility and embryonic survival. No adverse effects on female fertility and embryonic survival were evident in female animals dosed at 0.001 mg/kg/day (0.06% the human dose based on BSA in mg/m^2). Restoration of female fertility to values similar to controls was evident following a 29-day withdrawal period after dosing at 2 mg/kg/day (equivalent to the human dose based on BSA in mg/m^2). The effects of fulvestrant on the fertility of female rats appear to be consistent with its antiestrogenic activity. The potential effects of fulvestrant on the fertility of male animals were not studied, but in a 6-month toxicology study, male rats treated with intramuscular doses of 15 mg/kg/30 days, 10 mg/rat/30 days, or 10 mg/rat/15 days fulvestrant showed a loss of spermatozoa from the seminiferous tubules, seminiferous tubular atrophy, and degenerative changes in the epididymides. Changes in the testes and epididymides had not recovered 20 weeks after cessation of dosing. These fulvestrant doses correspond to 1.3-, 1.2-, and 3.5-fold the systemic exposure [AUC0-30 days] achieved in women receiving the recommended dose of 500 mg/month.

14 CLINICAL STUDIES

The efficacy of fulvestrant 500 mg versus fulvestrant 250 mg was compared in CONFIRM. The efficacy of fulvestrant 250 mg was compared to 1 mg anastrozole in Studies 0020 and 0021. The efficacy of fulvestrant 500 mg was compared to 1 mg anastrozole in FALCON. The efficacy of fulvestrant 500 mg in combination with palbociclib 125 mg was compared to fulvestrant 500 mg plus placebo in PALOMA- 3. The efficacy of fulvestrant 500 mg in combination with abemaciclib 150 mg was compared to fulvestrant 500 mg plus placebo in MONARCH 2. The efficacy of fulvestrant 500 mg in combination with ribociclib 600 mg was compared to fulvestrant 500 mg plus placebo in MONALEESA-3.

Monotherapy

Comparison of Fulvestrant Injection 500 mg and Fulvestrant Injection 250 mg (CONFIRM)

A randomized, double-blind, controlled clinical trial (CONFIRM, NCT00099437) was completed in 736 postmenopausal women with advanced breast cancer who had disease recurrence on or after adjuvant endocrine therapy or progression following endocrine therapy for advanced disease. This trial compared the efficacy and safety of fulvestrant 500 mg (n=362) with fulvestrant 250 mg (n=374).

Fulvestrant 500 mg was administered as two 5 mL injections each containing fulvestrant 250 mg/5 mL, one in each buttock, on Days 1, 15, 29, and every 28 (+/- 3) days thereafter. Fulvestrant 250 mg was administered as two 5 mL injections (one containing fulvestrant 250 mg/5 mL injection plus one placebo injection), one in each buttock, on Days 1, 15 (2 placebo injections only), 29, and every 28 (+/- 3) days thereafter.

The median age of study participants was 61 years. All patients had ER+ advanced breast cancer. Approximately 30% of subjects had no measurable disease. Approximately 55% of patients had visceral disease.

Results of CONFIRM are summarized in Table 12. The efficacy of fulvestrant 500 mg was compared to that of fulvestrant 250 mg. Figure 6 shows a Kaplan-Meier plot of the Progression Free Survival (PFS) data after a minimum follow-up duration of 18 months demonstrating statistically significant superiority of fulvestrant 500 mg vs. fulvestrant 250 mg. In the initial Overall Survival (OS) analysis after a minimum follow-up duration of 18 months, there was no statistically significant difference in OS between the two treatment groups. After a minimum follow-up duration of 50 months, an updated OS analysis was performed. Figure 7 shows a Kaplan-Meier plot of the updated OS data.

Table 12: Efficacy Results in CONFIRM (Intent-To-Treat (ITT) Population)
Endpoint | Fulvestrant 500 mg (N=362) | Fulvestrant 250 mg (N=374)
PFS^1 Median (months) | 6.5 | 5.4
Hazard Ratio^2 (95% CI^3) | 0.80 (0.68-0.94)
p-value | 0.006
OS^4 Updated Analysis^5 (% patients who died) | 261 (72.1%) | 293 (78.3%)
Median OS (months) | 26.4 | 22.3
Hazard Ratio^2 (95% CI^3)^6 | 0.81 (0.69-0.96)
ORR^7 (95% CI^3) | 13.8% (9.7%, 18.8%) (33/240) | 14.6% (10.5%, 19.4%) (38/261)
^1. PFS (Progression Free Survival)=the time between randomization and the earliest of progression or death from any cause. Minimum follow-up duration of 18 months.
^2. Hazard Ratio <1 favors fulvestrant 500 mg.
^3. CI=Confidence Interval
^4. OS=Overall Survival
^5. Minimum follow up duration of 50 months.
^6. Not statistically significant as no adjustments were made for multiplicity.
^7. ORR (Objective Response Rate), as defined as number (%) of patients with complete response or partial response, was analyzed in the evaluable patients with measurable disease at baseline (Fulvestrant 500 mg N=240; Fulvestrant 250 mg N=261). Minimum follow-up duration of 18 months.

Figure 6 Kaplan-Meier PFS: CONFIRM ITT Population

Figure 7 Kaplan-Meier OS (Minimum Follow-up Duration of 50 Months):
CONFIRM ITT Population

Comparison of Fulvestrant Injection 500 mg and Anastrozole 1 mg (FALCON)

A randomized, double-blind, double-dummy, multi-center study (FALCON, NCT01602380) of fulvestrant 500 mg versus anastrozole 1 mg was conducted in postmenopausal women with ER-positive and/or PgR-positive, HER2-negative locally advanced or metastatic breast cancer who had not previously been treated with any hormonal therapy. A total of 462 patients were randomized 1:1 to receive administration of fulvestrant 500 mg as an intramuscular injection on Days 1, 15, 29, and every 28 (+/- 3) days thereafter or daily administration of 1 mg of anastrozole orally. This study compared the efficacy and safety of fulvestrant 500 mg and anastrozole 1 mg.

Randomization was stratified by disease setting (locally advanced or metastatic), use of prior chemotherapy for advanced disease, and presence or absence of measurable disease.

The major efficacy outcome measure of the study was investigator-assessed progression-free survival (PFS) evaluated according to RECIST v.1.1 (Response Evaluation Criteria in Solid Tumors). Key secondary efficacy outcome measures included overall survival (OS), objective response rate (ORR), and duration of response (DoR).

Patients enrolled in this study had a median age of 63 years (range 36-90). The majority of patients (87%) had metastatic disease at baseline. Fifty-five percent (55%) of patients had visceral metastasis at baseline. A total of 17% of patients had received one prior chemotherapy regimen for advanced disease; 84% of patients had measurable disease. Sites of metastases were as follows: musculoskeletal 59%, lymph nodes 50%, respiratory 40%, liver (including gall bladder) 18%.

The efficacy results of FALCON are presented in Table 13 and Figure 8.

Table 13: Efficacy Results in FALCON (Investigator Assessment, ITT Population)
 | Fulvestrant | Anastrozole
 | 500 mg N=230 | 1 mg N=232
Progression-Free Survival
Number of PFS Events (%) | 143 (62.2%) | 166 (71.6%)
Median PFS (months) | 16.6 | 13.8
PFS Hazard Ratio (95% CI) | 0.797 (0.637- 0.999)
p-value | 0.049
Overall Survival^1
Number of OS Events | 67(29.1%) | 75 (32.3%)
Median OS (months) | NR | NR
OS Hazard Ratio (95% Cl) | 0.874 (0.629 - 1.216)
Objective Response for Patients with Measurable Disease | N=193 | N=196
Objective Response Rate (%, 95% CI) | 46.1% (38.9%, 53.4%) | 44.9% (37.8%, 52.1%)
Median DoR (months) | 20.0 | 13.2
NR: Not reached
^1. Interim OS analysis with 61% of total number of events required for the final OS analysis.

Figure 8 Kaplan-Meier Plot of Progression-Free Survival
(Investigator Assessment, ITT Population) ─ FALCON

Comparison of Fulvestrant Injection 250 mg and Anastrozole 1 mg in Combined Data (Studies 0020 and 0021)

Efficacy of fulvestrant was established by comparison to the selective aromatase inhibitor anastrozole in two randomized, controlled clinical trials (one conducted in North America, Study 0021, NCT00635713; the other predominantly in Europe, Study 0020) in postmenopausal women with locally advanced or metastatic breast cancer. All patients had progressed after previous therapy with an antiestrogen or progestin for breast cancer in the adjuvant or advanced disease setting.

The median age of study participants was 64 years. 81.6% of patients had ER+ and/or PgR+ tumors. Patients with ER-/PgR- or unknown tumors were required to have demonstrated a prior response to endocrine therapy. Sites of metastases occurred as follows: visceral only 18.2%; viscera – liver involvement 23.0%; lung involvement 28.1%; bone only 19.7%; soft tissue only 5.2%; skin and soft tissue 18.7%.

In both trials, eligible patients with measurable and/or evaluable disease were randomized to receive either fulvestrant 250 mg intramuscularly once a month (28 days ± 3 days) or anastrozole 1 mg orally once a day. All patients were assessed monthly for the first three months and every three months thereafter. Study 0021 was a double-blind, randomized trial in 400 postmenopausal women. Study 0020 was an open-label, randomized trial conducted in 451 postmenopausal women. Patients on the fulvestrant arm of Study 0021 received two separate injections (2 x 2.5 mL), whereas fulvestrant patients received a single injection (1 x 5 mL) in Study 0020. In both trials, patients were initially randomized to a 125 mg per month dose as well, but interim analysis showed a very low response rate, and low dose groups were dropped.

Results of the trials, after a minimum follow-up duration of 14.6 months, are summarized in Table 14. The effectiveness of fulvestrant 250 mg was determined by comparing Objective Response Rate (ORR) and Time to Progression (TTP) results to anastrozole 1 mg, the active control. The two studies ruled out (by one-sided 97.7% confidence limit) inferiority of fulvestrant to anastrozole of 6.3% and 1.4% in terms of ORR. There was no statistically significant difference in overall survival (OS) between the two treatment groups after a follow-up duration of 28.2 months in Study 0021 and 24.4 months in Study 0020.

Table 14: Efficacy Results in Studies 0020 and 0021 (Objective Response Rate (ORR) and Time to Progression (TTP))
 | Study 0021 (Double-Blind) |  | Study 0020 (Open-Label)
 | Fulvestrant | Anastrozole | Fulvestrant |  | Anastrozole
Endpoint | 250 mg N=206 | 1 mg N=194 | 250 mg N=222 |  | 1 mg N=229
Objective Tumor Response Number (%) of subjects with CR^1 + PR^2 | 35 (17.0) | 33 (17.0) | 45 (20.3) |  | 34 (14.9)
% Difference in Tumor Response Rate (FUL^3-ANA^4) 2–sided 95.4% CI^5 | 0.0 (-6.3, 8.9) |  | 5.4 (-1.4, 14.8)
Time to Progression (TTP) Median TTP (days) | 165 | 103 | 166 |  | 156
Hazard Ratio^6 2-sided 95.4% CI | 0.9 (0.7, 1.1) |  | 1.0 (0.8, 1.2)
Stable Disease for ≥24 weeks (%) | 26.7 | 19.1 | 24.3 |  | 30.1
Overall Survival (OS)
Died n (%) Median Survival (days) | 152 (73.8%) 844 | 149 (76.8%) 913 | 167 (75.2%) 803 |  | 173 (75.5%) 736
Hazard Ratio^6 (2-sided 95% CI) | 0.98 (0.78, 1.24) |  | 0.97 (0.78, 1.21)
^1. CR=Complete Response
^2. PR=Partial Response
^3. FUL=fulvestrant
^4. ANA=anastrozole
^5. CI=Confidence Interval
^6. Hazard Ratio <1 favors fulvestrant

Combination Therapy Patients with HR-positive, HER2-negative advanced or metastatic breast cancer who have had disease progression on or after prior adjuvant or metastatic endocrine therapy

Fulvestrant Injection 500 mg in Combination with Palbociclib 125 mg (PALOMA-3)

PALOMA-3 (NCT-1942135) was an international, randomized, double-blind, parallel group, multicenter study of fulvestrant plus palbociclib versus fulvestrant plus placebo conducted in women with HR-positive, HER2-negative advanced breast cancer, regardless of their menopausal status, whose disease progressed on or after prior endocrine therapy.

A total of 521 pre/postmenopausal women were randomized 2:1 to fulvestrant plus palbociclib or fulvestrant plus placebo and stratified by documented sensitivity to prior hormonal therapy, menopausal status at study entry (pre/peri versus postmenopausal), and presence of visceral metastases. Palbociclib was given orally at a dose of 125 mg daily for 21 consecutive days followed by 7 days off treatment. Fulvestrant 500 mg was administered as two 5 mL injections each containing fulvestrant 250 mg/5 mL, one in each buttock, on Days 1, 15, 29, and every 28 (+/- 3) days thereafter. Pre/perimenopausal women were enrolled in the study and received the LHRH agonist goserelin for at least 4 weeks prior to and for the duration of PALOMA-3.

Patients continued to receive assigned treatment until objective disease progression, symptomatic deterioration, unacceptable toxicity, death, or withdrawal of consent, whichever occurred first. The major efficacy outcome of the study was investigator-assessed PFS evaluated according to RECIST v.1.1.

Patients enrolled in this study had a median age of 57 years (range 29 to 88). The majority of patients on study were White (74%), all patients had an ECOG PS of 0 or 1, and 80% were postmenopausal. All patients had received prior systemic therapy and 75% of patients had received a previous chemotherapy regimen. Twenty-five percent of patients had received no prior therapy in the metastatic disease setting, 60% had visceral metastases, and 23% had bone only disease.

The results from the investigator-assessed PFS and final OS data from PALOMA-3 are summarized in Table 15. The relevant Kaplan-Meier plots are shown in Figures 9 and 10, respectively. Consistent PFS results were observed across patient subgroups of disease site, sensitivity to prior hormonal therapy, and menopausal status. After a median follow-up time of 45 months, the final OS results were not statistically significant.

Table 15: Efficacy Results in PALOMA-3 (Investigator Assessment, ITT Population)
 | Fulvestrant plus Palbociclib | Fulvestrant plus Placebo
Progression-Free Survival for ITT | N=347 | N=174
Number of PFS Events (%) | 145 (41.8%) | 114 (65.5%)
Median PFS (months) (95% CI) | 9.5 (9.2-11.0) | 4.6 (3.5-5.6)
Hazard Ratio (95% CI) and p-value | 0.461 (0.360-0.591) p <0.0001
Objective Response for Patients with Measurable Disease | N=267 | N=138
Objective response rate^1 (%, 95% CI) | 24.6 (19.6-30.2) | 10.9 (6.2-17.3)
Overall Survival for ITT population | N=347 | N=174
Number of OS events (%) | 201 (57.9) | 109 (62.6)
Median OS (months) (95% CI) | 34.9 (28.8, 40.0) | 28.0 (23.6, 34.6)
Hazard Ratio (95% CI) and p-value | 0.814 (0.644, 1.029), p=0.0857^2,3
N=number of patients; PFS=progression-free survival; CI=confidence interval; ITT=Intent-to-Treat; OS=overall survival.
1. Responses are based on confirmed responses.
2. Not statistically significant at the pre-specified 2-sided alpha level of 0.047.
3. 2-sided p-value from the log-rank test stratified by the presence of visceral metastases and sensitivity to prior endocrine therapy per randomization.

Figure 9 Kaplan-Meier Plot of Progression-Free Survival
(Investigator Assessment, ITT Population) ─ PALOMA-3

Figure 10 Kaplan-Meier Plot of Overall Survival (ITT Population) ─ PALOMA-3

FUL=fulvestrant; PAL=palbociclib; PCB=placebo.

Fulvestrant Injection 500 mg in Combination with Abemaciclib 150 mg (MONARCH 2)

MONARCH 2 (NCT02107703) was a randomized, placebo-controlled, multi-center study conducted in women with HR-positive, HER2-negative metastatic breast cancer with disease progression following endocrine therapy treated with fulvestrant plus abemaciclib versus fulvestrant plus placebo.

Randomization was stratified by disease site (visceral, bone only, or other) and by sensitivity to prior endocrine therapy (primary or secondary resistance). A total of 669 patients received intramuscular injection of fulvestrant 500 mg on Days 1 and 15 of cycle 1 and then on Day 1 of cycle 2 and beyond (28-day cycles), plus abemaciclib or placebo orally twice daily.

Pre/perimenopausal women were enrolled in the study and received the gonadotropin-releasing hormone agonist goserelin for at least 4 weeks prior to and for the duration of MONARCH 2. Patients remained on continuous treatment until development of progressive disease or unmanageable toxicity.

Patient median age was 60 years (range, 32-91 years), and 37% of patients were older than 65. The majority were White (56%), and 99% of patients had an Eastern Cooperative Oncology Group (ECOG) performance status of 0 or 1. Twenty percent (20%) of patients had de novo metastatic disease, 27% had bone only disease, and 56% had visceral disease. Twenty-five percent (25%) of patients had primary endocrine therapy resistance. Seventeen percent (17%) of patients were pre- or perimenopausal.

The efficacy results from the MONARCH 2 study are summarized in Table 16, Figure 11, and Figure 12. PFS assessment based on a blinded independent radiologic review was consistent with the investigator assessment. Consistent results were observed across patient stratification subgroups of disease site and endocrine therapy resistance for PFS and OS.

Table 16: Efficacy Results in MONARCH 2 (Intent-to-Treat Population)
 | Fulvestrant plus Abemaciclib | Fulvestrant plus Placebo
Progression-Free Survival (Investigator Assessment) | N=446 | N=223
Number of patients with an event (n, %) | 222 (49.8) | 157 (70.4)
Median (months, 95% CI) | 16.4 (14.4, 19.3) | 9.3 (7.4, 12.7)
Hazard ratio (95% CI)^1 | 0.553 (0.449, 0.681)
p-value^1 | p<0.0001
Overall Survival^2
Number of deaths (n, %) | 211 (47.3) | 127 (57.0)
Median OS in months (95% CI) | 46.7 (39.2, 52.2) | 37.3 (34.4, 43.2)
Hazard ratio (95% CI)^1 | 0.757 (0.606, 0.945)
p-value^1 | p=0.0137
Objective Response for Patients with Measurable Disease | N=318 | N=164
Objective response rate^3 (n, %) | 153 (48.1) | 35 (21.3)
95% CI | 42.6, 53.6 | 15.1, 27.6
Abbreviations: CI=confidence interval, OS=overall survival.
^1.Stratified by disease site (visceral metastases vs. bone-only metastases vs. other) and endocrine therapy resistance (primary resistance vs. secondary resistance)
^2.Data from a pre-specified interim analysis (77% of the number of events needed for the planned final analysis) with the p-value compared with the allocated alpha of 0.021.
^3.Complete response + partial response.

Figure 11 Kaplan-Meier Curves of Progression-Free Survival:
Fulvestrant Injection Plus Abemaciclib versus Fulvestrant Injection plus Placebo (MONARCH 2)

Figure 12 Kaplan-Meier Curves of Overall Survival: Fulvestrant plus Abemaciclib versus Fulvestrant plus Placebo (MONARCH 2)

Postmenopausal women with HR-positive, HER2-negative advanced or metastatic breast cancer for initial endocrine based therapy or after disease progression on endocrine therapy

Fulvestrant Injection 500 mg in Combination with Ribociclib 600 mg (MONALEESA-3)

MONALEESA-3 (NCT 02422615) was a randomized double-blind, placebo-controlled study of fulvestrant plus ribociclib versus fulvestrant plus placebo conducted in postmenopausal women with hormone receptor positive, HER2-negative, advanced breast cancer who have received no or only one line of prior endocrine treatment.

A total of 726 patients were randomized in a 2:1 ratio to receive fulvestrant plus ribociclib or fulvestrant plus placebo and stratified according to the presence of liver and/or lung metastases and prior endocrine therapy for advanced or metastatic disease. Fulvestrant 500 mg was administered intramuscularly on Days 1, 15, 29, and once monthly thereafter, with either ribociclib 600 mg or placebo given orally once daily for 21 consecutive days followed by 7 days off until disease progression or unacceptable toxicity. The major efficacy outcome measure for the study was investigator-assessed progression-free survival (PFS) using Response Evaluation Criteria in Solid Tumors (RECIST) v1.1.

Patients enrolled in this study had a median age of 63 years (range 31 to 89). Of the patients enrolled, 47% were 65 years and older, including 14% age 75 years and older. The patients enrolled were primarily Caucasian (85%), Asian (9%), and Black (0.7%). Nearly all patients (99.7%) had an ECOG performance status of 0 or 1. First- and second-line patients were enrolled in this study (of which 19% had de novo metastatic disease). Forty-three percent (43%) of patients had received chemotherapy in the adjuvant vs. 13% in the neoadjuvant setting and 59% had received endocrine therapy in the adjuvant vs. 1% in the neoadjuvant setting prior to study entry. Twenty-one percent (21%) of patients had bone-only disease and 61% had visceral disease. Demographics and baseline disease characteristics were balanced and comparable between study arms.

The efficacy results from MONALEESA-3 are summarized in Table 17, Figure 13, and Figure 14. Consistent results were observed in stratification factor subgroups of disease site and prior endocrine treatment for advanced disease.

Table 17: Efficacy Results – MONALEESA-3 (Investigator Assessment, Intent-to-Treat Population)
 | Fulvestrant plus Ribociclib | Fulvestrant plus Placebo
Progression-free survival* | N=484 | N=242
Events (n, %) | 210 (43.4%) | 151 (62.4%)
Median (months, 95% CI) | 20.5 (18.5, 23.5) | 12.8 (10.9, 16.3)
Hazard Ratio (95% CI) | 0.593 (0.480 to 0.732)
p-value^1 | <0.0001
Overall Survival | N=484 | N=242
Events (n, %) | 167 (34.5%) | 108 (44.6%)
Median (months, 95% CI) | NR (42.5, NR) | 40.0 (37.0, NR)
Hazard Ratio (95% CI) | 0.724 (0.568, 0.924)
p-value^1 | 0.00455
Overall Response Rate 2* | N=379 | N=181
Patients with measurable disease (95% CI) | 40.9 (35.9, 45.8) | 28.7 (22.1, 35.3)
Abbreviation: NR, not reached
^1. p-value is obtained from the one-sided log-rank
^2. Based on confirmed responses
* Investigator Assessment

Figure 13 Kaplan-Meier Progression Free Survival Curves – MONALEESA-3 (Intent-To-Treat
Population, Investigator assessment)

Figure 14 Kaplan-Meier plot of Overall Survival – MONALEESA-3 (Intent-to-Treat Population)

16 HOW SUPPLIED/STORAGE AND HANDLING

Fulvestrant Injection is supplied as two 5 mL clear glass (Type 1) syringes fitted with a removable tip cap, each containing 250 mg per 5 mL of Fulvestrant Injection solution for intramuscular use.

Product Code | Unit of Sale | Strength | Each
760105 | NDC 63323-715-05 Unit of 2 | 250 mg per 5 mL (50 mg per mL) | NDC 63323-715-01 5 mL Single-Dose Pre-filled Syringe

The pre-filled syringes with attached plunger rods are presented in a tray with two pre-packaged safety needles (SafetyGlide™) for connection to the syringes.

Discard each syringe after use. If a patient dose requires only one syringe, unused syringe should be stored as directed below.

Storage:

Store at 20°C to 25°C (68°F to 77°F) with excursions permitted between 15°C to 30°C (59°F to 86°F) [USP Controlled Room Temperature].

Do not freeze. Do not use Fulvestrant Injection if it has been frozen. To protect from light, store in the original carton until time of use.

17 PATIENT COUNSELING INFORMATION

Advise the patient to read the FDA-approved patient labeling (Patient Information).

Monotherapy

Risk of Bleeding:

- Because Fulvestrant Injection is administered intramuscularly, it should be used with caution in patients with bleeding disorders, decreased platelet count, or in patients receiving anticoagulants (for example, warfarin) [see Warnings and Precautions (5.1)].

Embryo-Fetal Toxicity:

- Advise females of reproductive potential of the potential risk to a fetus and to use effective contraception during treatment with Fulvestrant Injection and for one year after the last dose. Advise females to inform their healthcare provider of a known or suspected pregnancy [see Warnings and Precautions (5.4) and Use in Specific Populations (8.1), (8.3)].

Lactation:

- Advise women not to breastfeed during treatment with Fulvestrant Injection and for one year after the last dose [see Use in Specific Populations (8.2)].

Combination Therapy

When Fulvestrant Injection is used in combination with palbociclib, abemaciclib, or ribociclib, refer to the respective Full Prescribing Information for Patient Counseling Information.

Manufactured for:

Lake Zurich, IL 60047
www.fresenius-kabi.com/us
Made in Austria

451542D

PATIENT INFORMATION
Fulvestrant (ful-VES-trant)
Injection

What is Fulvestrant Injection?
Fulvestrant Injection is a prescription medicine used to treat advanced breast cancer or breast cancer that has spread to other parts of the body (metastatic).
Fulvestrant Injection may be used alone, if you have gone through menopause, and your advanced breast cancer is:

- hormone receptor (HR)-positive and human epidermal growth factor receptor 2 (HER2)-negative and has not been previously treated with endocrine therapy or
- HR-positive and has progressed after endocrine therapy.

Fulvestrant Injection may be used in combination with ribociclib, if you have gone through menopause, and your advanced or metastatic breast cancer is HR-positive and HER2-negative, and has not been previously treated with endocrine therapy or has progressed after endocrine therapy.
Fulvestrant Injection may be used in combination with palbociclib or abemaciclib if your advanced or metastatic breast cancer is HR-positive and HER2-negative, and has progressed after endocrine therapy.
When Fulvestrant Injection is used in combination with palbociclib, abemaciclib, or ribociclib, also read the Patient Information for the prescribed product.
It is not known if Fulvestrant Injection is safe and effective in children.
It is not known if Fulvestrant Injection is safe and effective in people with severe liver problems.

Who should not receive Fulvestrant Injection?
Do not receive Fulvestrant Injection if you have had an allergic reaction to fulvestrant or any of the ingredients in Fulvestrant Injection. See the end of this leaflet for a list of the ingredients in Fulvestrant Injection.
Symptoms of an allergic reaction to Fulvestrant Injection may include:

- itching or hives
- swelling of your face, lips, tongue, or throat
- trouble breathing

What should I tell my healthcare provider before receiving Fulvestrant Injection?
Before receiving Fulvestrant Injection, tell your healthcare provider about all of your medical conditions, including if you:

- have a low level of platelets in your blood or bleed easily.
- have liver problems.
- are pregnant or plan to become pregnant.
- Fulvestrant Injection can harm your unborn baby. Females who are able to become pregnant:
  - Your healthcare provider may perform a pregnancy test within 7 days before you start Fulvestrant Injection.
  - You should use effective birth control during treatment with Fulvestrant Injection and for one year after the last dose of Fulvestrant Injection.
  - Tell your healthcare provider right away if you become pregnant or think you are pregnant during treatment with Fulvestrant Injection.
- are breastfeeding or plan to breastfeed. It is not known if Fulvestrant Injection passes into your breast milk. Do not breastfeed during your treatment with Fulvestrant Injection and for one year after the last dose of Fulvestrant Injection. Talk to your healthcare provider about the best way to feed your baby during this time.

Tell your healthcare provider about all the medicines you take, including prescription and over-the-counter medicines, vitamins, and herbal supplements. Fulvestrant Injection may affect the way other medicines work, and other medicines may affect how Fulvestrant Injection works.
Especially tell your healthcare provider if you take a blood thinner medicine.

How will I receive Fulvestrant Injection?

- Your healthcare provider will give you Fulvestrant Injection by injection into the muscle of each buttock.
- Your healthcare provider may change your dose of Fulvestrant Injection if needed.

What are the possible side effects of Fulvestrant Injection?
Fulvestrant Injection may cause serious side effects, including:

- Injection site related nerve damage. Call your healthcare provider if you develop any of the following symptoms in your legs following a Fulvestrant Injection:
  - numbness
  - tingling
  - weakness

The most common side effects of Fulvestrant Injection include:

- injection site pain
- nausea
- muscle, joint, and bone pain
- headache
- back pain
- tiredness
- pain in arms, hands, legs, or feet
- hot flashes

- vomiting
- loss of appetite
- weakness
- cough
- shortness of breath
- constipation
- increased liver enzymes
- diarrhea

Fulvestrant Injection may cause fertility problems in males and females. Talk to your healthcare provider if you plan to become pregnant.
Tell your healthcare provider if you have any side effect that bothers you or that does not go away. These are not all of the possible side effects with Fulvestrant Injection. For more information, ask your healthcare provider or pharmacist.
Call your healthcare provider for medical advice about side effects. You may report side effects to FDA at 1-800-FDA1088.

General information about the safe and effective use of Fulvestrant Injection.
Medicines are sometimes prescribed for purposes other than those listed in a Patient Information leaflet. If you would like more information, talk with your healthcare provider. You can ask your pharmacist or healthcare provider for information about Fulvestrant Injection that is written for health professionals.

What are the ingredients in Fulvestrant Injection?
Active ingredient: fulvestrant.
Inactive ingredients: dehydrated alcohol, benzyl alcohol, polysorbate 80, alpha-tocopherol, and castor oil.
SafetyGlideTM is a trademark of Becton Dickinson and Company. Manufactured for:
Lake Zurich, IL 60047
Made in Austria
451556C
Revised: September 2021
For more information, go to www.fresenius-kabi.com/us or call 1-800-551-7176.
This Patient Information has been approved by the U.S. Food and Drug Administration.

PACKAGE LABEL

Principal Display Panel – Fulvestrant Injection 250 mg per 5 mL Syringe Carton Panel

For Single-Dose Only NDC 63323-715-05

Fulvestrant Injection

250 mg per 5 mL (50 mg per mL)

For intramuscular use only.

PACKAGE LABEL

Principal Display Panel – Fulvestrant Injection 250 mg per 5 mL Syringe Label

NDC 63323-715-01

Fulvestrant Injection

250 mg per 5 mL (50 mg per mL)

For intramuscular use only.